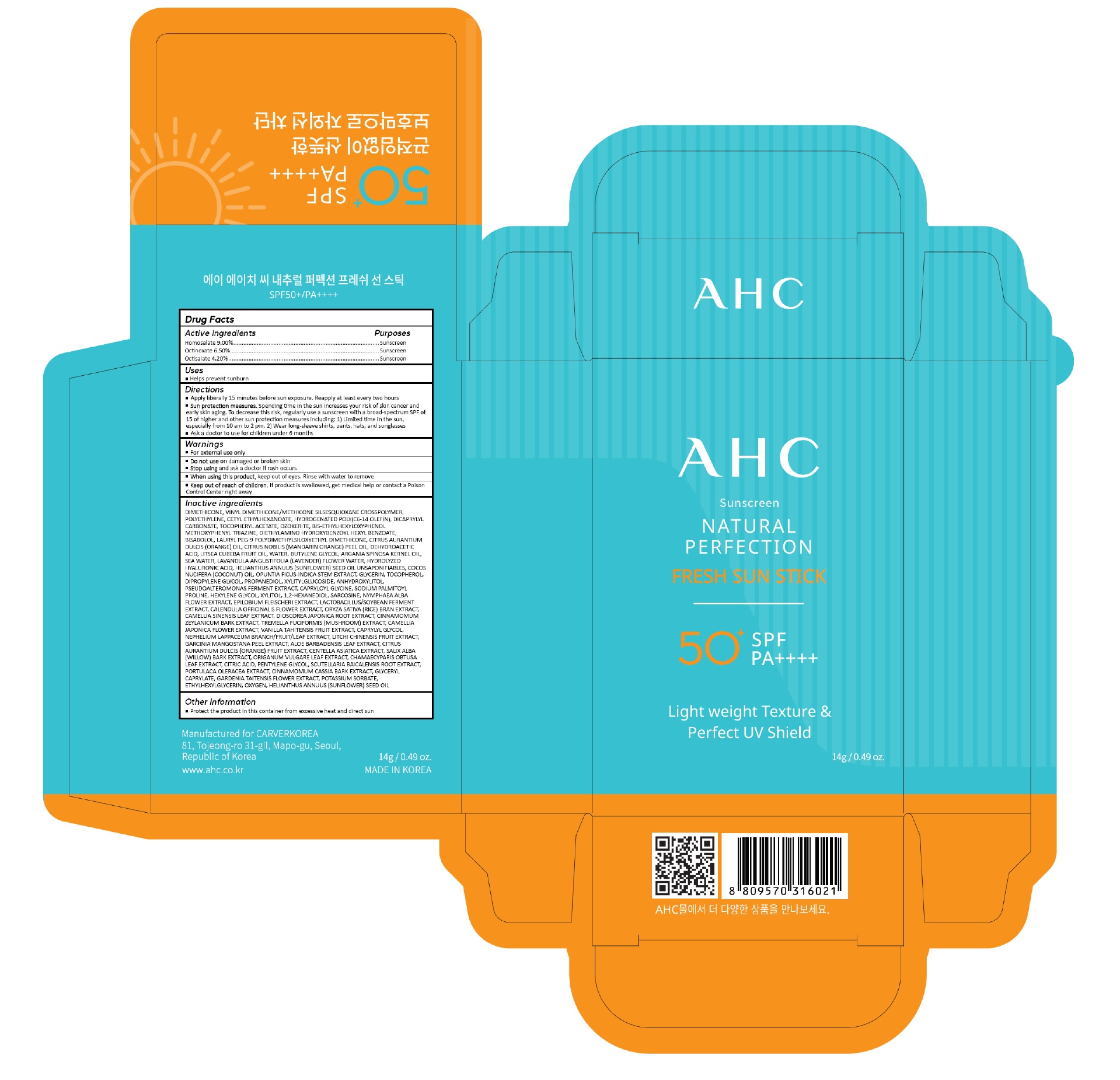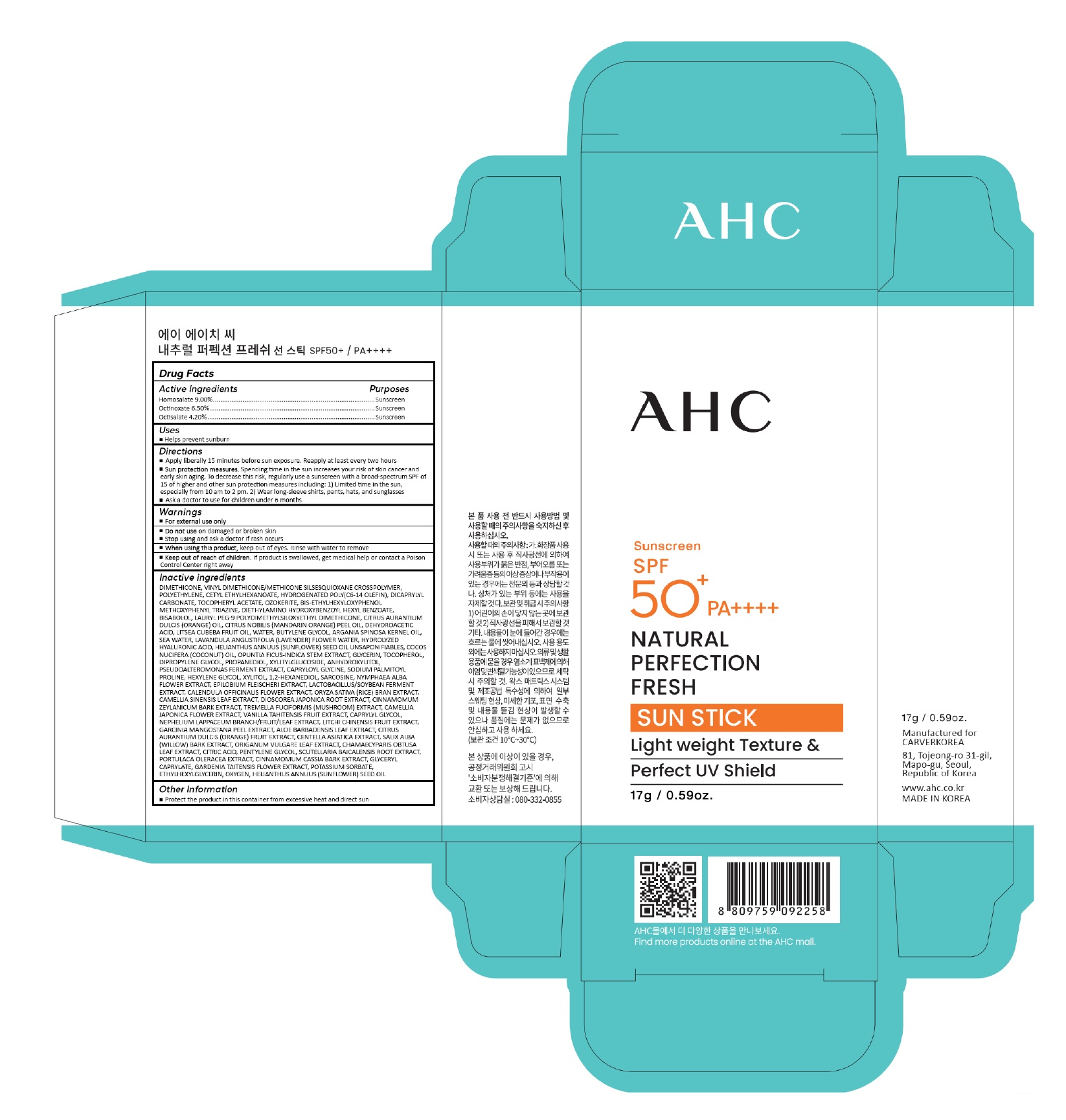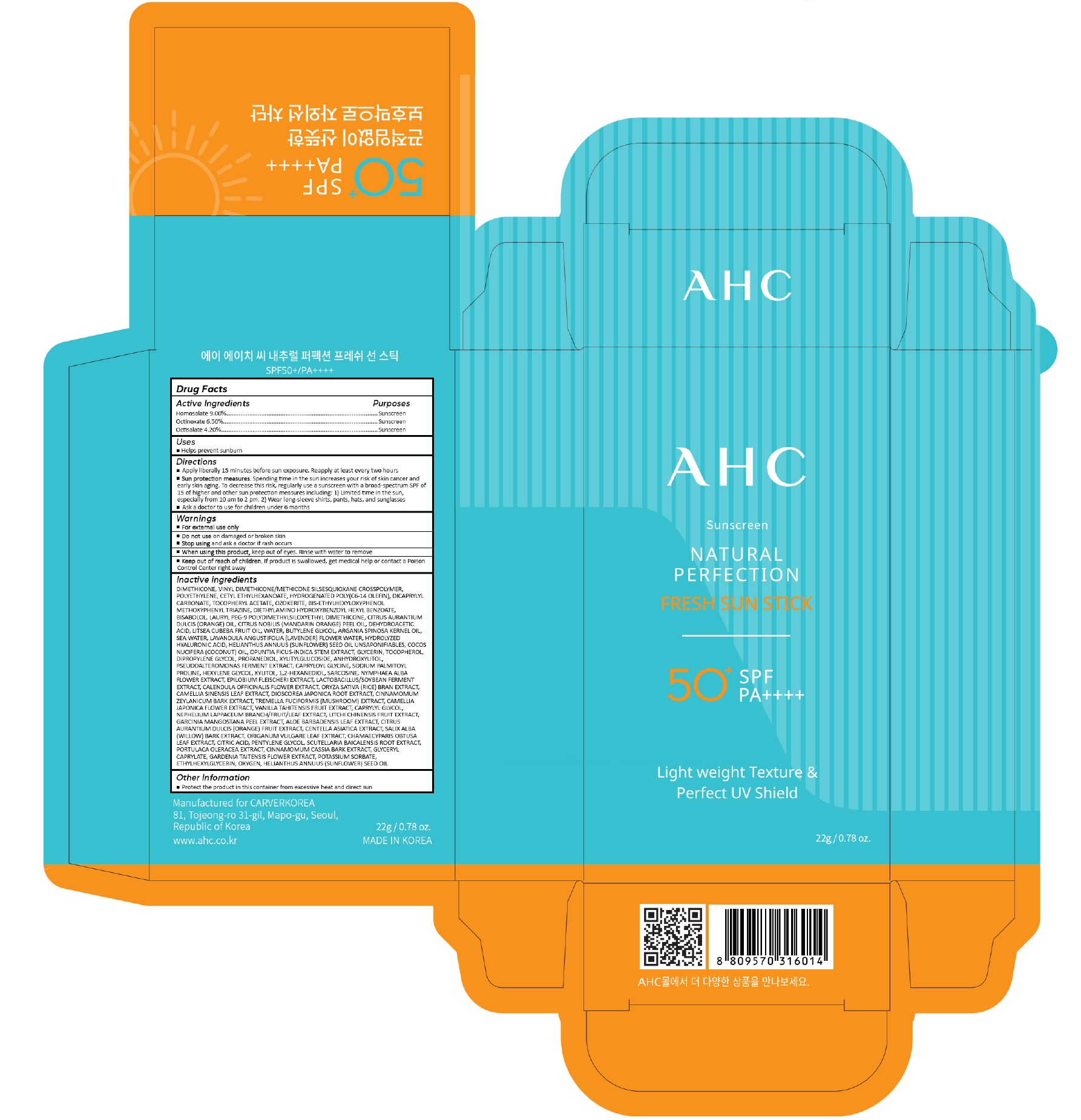 DRUG LABEL: AHC Natural Perfection Fresh Sun stick
NDC: 58930-201 | Form: STICK
Manufacturer: CARVERKOREA Co.,Ltd.
Category: otc | Type: HUMAN OTC DRUG LABEL
Date: 20230613

ACTIVE INGREDIENTS: HOMOSALATE 9 g/100 g; OCTINOXATE 6.5 g/100 g; OCTISALATE 4.2 g/100 g
INACTIVE INGREDIENTS: DIMETHICONE; VINYL DIMETHICONE/METHICONE SILSESQUIOXANE CROSSPOLYMER; HIGH DENSITY POLYETHYLENE; CETYL ETHYLHEXANOATE; HYDROGENATED POLY(C6-14 OLEFIN; 4 CST); DICAPRYLYL CARBONATE; .ALPHA.-TOCOPHEROL ACETATE; CERESIN; BEMOTRIZINOL; DIETHYLAMINO HYDROXYBENZOYL HEXYL BENZOATE; LEVOMENOL; LAURYL PEG-9 POLYDIMETHYLSILOXYETHYL DIMETHICONE; ORANGE OIL, COLD PRESSED; MANDARIN OIL; DEHYDROACETIC ACID; LITSEA OIL; WATER; BUTYLENE GLYCOL; ARGAN OIL; SODIUM CHLORIDE; LAVENDER OIL; SUNFLOWER OIL UNSAPONIFIABLES; COCONUT OIL; OPUNTIA FICUS-INDICA STEM; GLYCERIN; TOCOPHEROL; DIPROPYLENE GLYCOL; PROPANEDIOL; XYLITYLGLUCOSIDE; ANHYDROXYLITOL; CAPRYLOYL GLYCINE; SODIUM PALMITOYL PROLINE; HEXYLENE GLYCOL; XYLITOL; 1,2-HEXANEDIOL; SARCOSINE; NYMPHAEA ALBA FLOWER; CALENDULA OFFICINALIS FLOWER; RICE BRAN; GREEN TEA LEAF; DIOSCOREA JAPONICA TUBER; CINNAMON BARK OIL; TREMELLA FUCIFORMIS FRUITING BODY; CAMELLIA JAPONICA FLOWER; TAHITIAN VANILLA BEAN; CAPRYLYL GLYCOL; LITCHI FRUIT; GARCINIA MANGOSTANA FRUIT RIND; ALOE VERA LEAF; ORANGE; CENTELLA ASIATICA TRITERPENOIDS; SALIX ALBA BARK; OREGANO; CHAMAECYPARIS OBTUSA LEAF; CITRIC ACID MONOHYDRATE; PENTYLENE GLYCOL; SCUTELLARIA BAICALENSIS ROOT; PURSLANE; CHINESE CINNAMON; GLYCERYL MONOCAPRYLATE; GARDENIA TAITENSIS FLOWER; POTASSIUM SORBATE; ETHYLHEXYLGLYCERIN; OXYGEN; SUNFLOWER OIL

58930-201_AHC Natural Perfection Fresh Sun Stick

ACTIVE INGREDIENT

Homosalate 9.00%
Octinoxate 6.50%
Octisalate 4.20%

PURPOSE

Sunscreen

INDICATIONS AND USAGE

Helps prevent sunburn

DOSAGE AND ADMINISTRATION

Apply liberally 15 minutes before sun exposure. Reapply at least every two hours

Sun protection measures. Spending time in the sun increases your risk of skin cancer and early skin aging. To decrease this risk, regularly use a sunscreen with a broad spectrum SPF of 15 of higher and other sun protection measures including: 1) Limited time in the sun, especially from 10 am to 2 pm. 2) Wear long-sleeve shirts, pants, hats, and sunglasses

Ask a doctor to use for children under 6 months

WARNINGS

For external use only

Do not use on damaged or broken skin

Stop using and ask a doctor if rash occurs

When using this product, keep out of eyes. Rinse with water to remove

Keep out of reach of children. If product is swallowed, get medical help or contact a Poison Control Center right away

INACTIVE INGREDIENT

DIMETHICONE, VINYL DIMETHICONE/METHICONE SILSESQUIOXANE CROSSPOLYMER, POLYETHYLENE, CETYL ETHYLHEXANOATE, HYDROGENATED POLY(C6-14 OLEFIN), DICAPRYLYL CARBONATE, TOCOPHERYL ACETATE, OZOKERITE, BIS-ETHYLHEXYLOXYPHENOL METHOXYPHENYL TRIAZINE, DIETHYLAMINO HYDROXYBENZOYL HEXYL BENZOATE, BISABOLOL, LAURYL PEG-9 POLYDIMETHYLSILOXYETHYL DIMETHICONE, CITRUS AURANTIUM DULCIS (ORANGE) OIL, CITRUS NOBILIS (MANDARIN ORANGE) PEEL OIL, DEHYDROACETIC ACID, LITSEA CUBEBA FRUIT OIL, WATER, BUTYLENE GLYCOL, ARGANIA SPINOSA KERNEL OIL, SEA WATER, LAVANDULA ANGUSTIFOLIA (LAVENDER) FLOWER WATER, HYDROLYZED HYALURONIC ACID, HELIANTHUS ANNUUS (SUNFLOWER) SEED OIL UNSAPONIFIABLES, COCOS NUCIFERA (COCONUT) OIL, OPUNTIA FICUS-INDICA STEM EXTRACT, GLYCERIN, TOCOPHEROL, DIPROPYLENE GLYCOL, PROPANEDIOL, XYLITYLGLUCOSIDE, ANHYDROXYLITOL, PSEUDOALTEROMONAS FERMENT EXTRACT, CAPRYLOYL GLYCINE, SODIUM PALMITOYL PROLINE, HEXYLENE GLYCOL, XYLITOL, 1,2-HEXANEDIOL, SARCOSINE, NYMPHAEA ALBA FLOWER EXTRACT, EPILOBIUM FLEISCHERI EXTRACT, LACTOBACILLUS/SOYBEAN FERMENT EXTRACT, CALENDULA OFFICINALIS FLOWER EXTRACT, ORYZA SATIVA (RICE) BRAN EXTRACT, CAMELLIA SINENSIS LEAF EXTRACT, DIOSCOREA JAPONICA ROOT EXTRACT, CINNAMOMUM ZEYLANICUM BARK EXTRACT, TREMELLA FUCIFORMIS (MUSHROOM) EXTRACT, CAMELLIA JAPONICA FLOWER EXTRACT, VANILLA TAHITENSIS FRUIT EXTRACT, CAPRYLYL GLYCOL, NEPHELIUM LAPPACEUM BRANCH/FRUIT/LEAF EXTRACT, LITCHI CHINENSIS FRUIT EXTRACT, GARCINIA MANGOSTANA PEEL EXTRACT, ALOE BARBADENSIS LEAF EXTRACT, CITRUS AURANTIUM DULCIS (ORANGE) FRUIT EXTRACT, CENTELLA ASIATICA EXTRACT, SALIX ALBA (WILLOW) BARK EXTRACT, ORIGANUM VULGARE LEAF EXTRACT, CHAMAECYPARIS OBTUSA LEAF EXTRACT, CITRIC ACID, PENTYLENE GLYCOL, SCUTELLARIA BAICALENSIS ROOT EXTRACT, PORTULACA OLERACEA EXTRACT, CINNAMOMUM CASSIA BARK EXTRACT, GLYCERYL CAPRYLATE, GARDENIA TAITENSIS FLOWER EXTRACT, POTASSIUM SORBATE, ETHYLHEXYLGLYCERIN, OXYGEN, HELIANTHUS ANNUUS (SUNFLOWER) SEED OIL